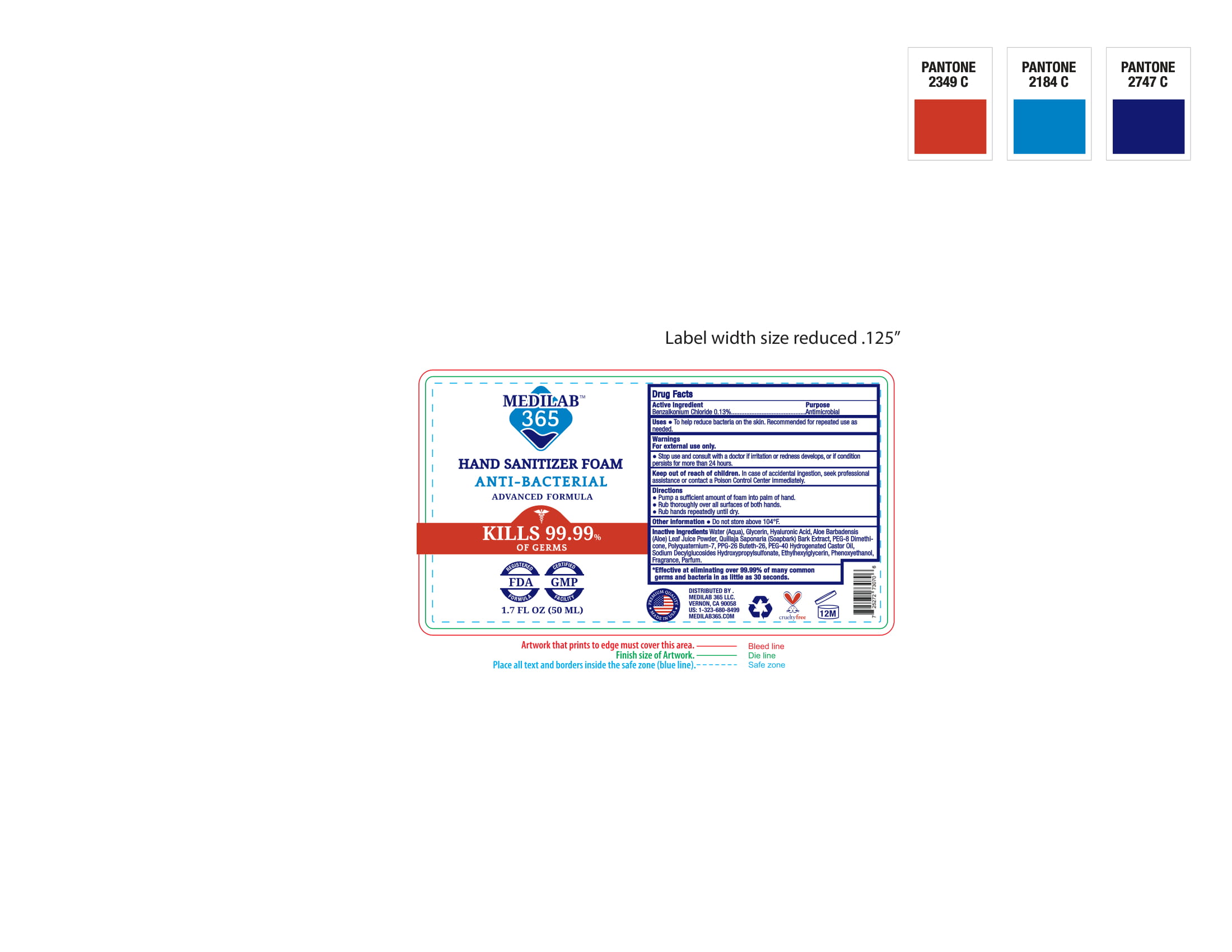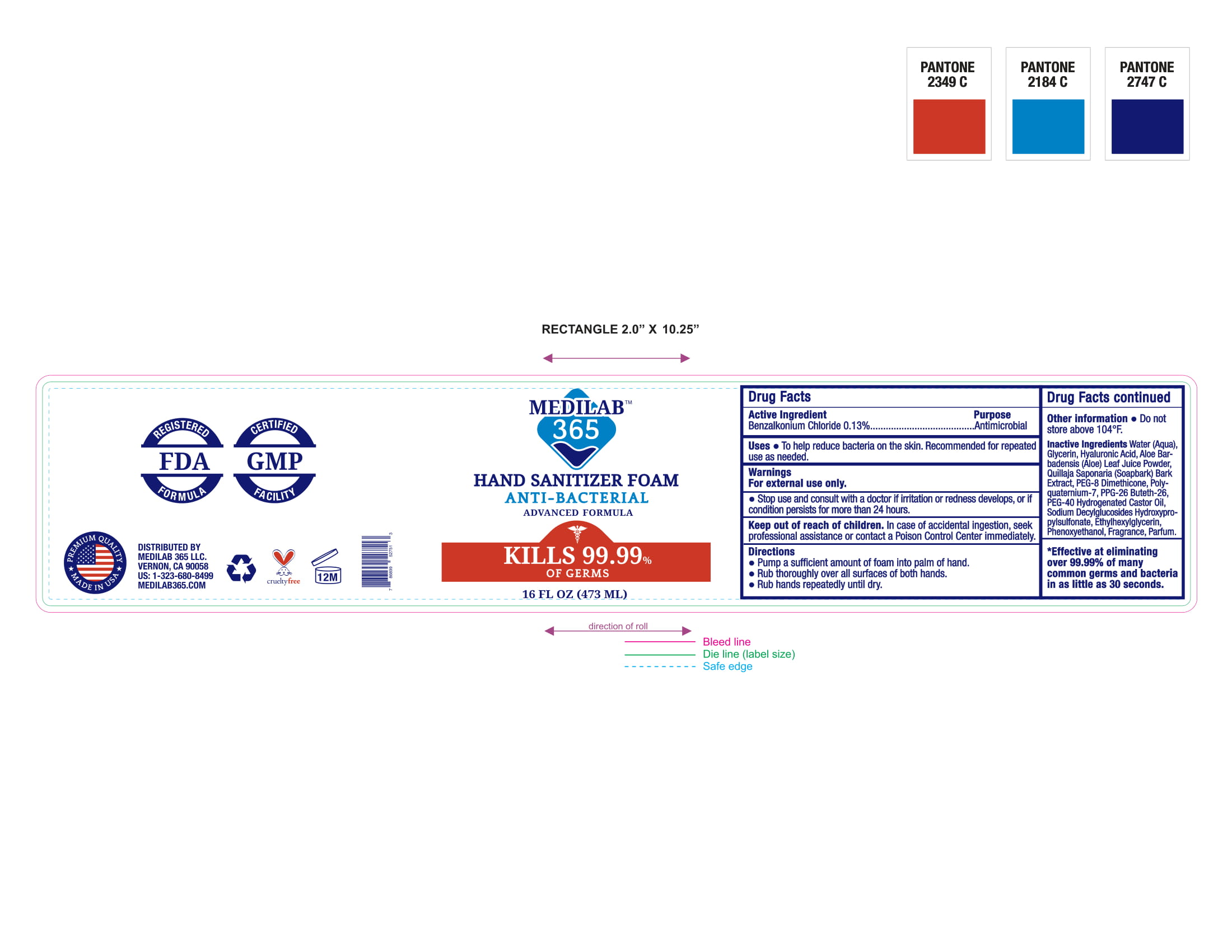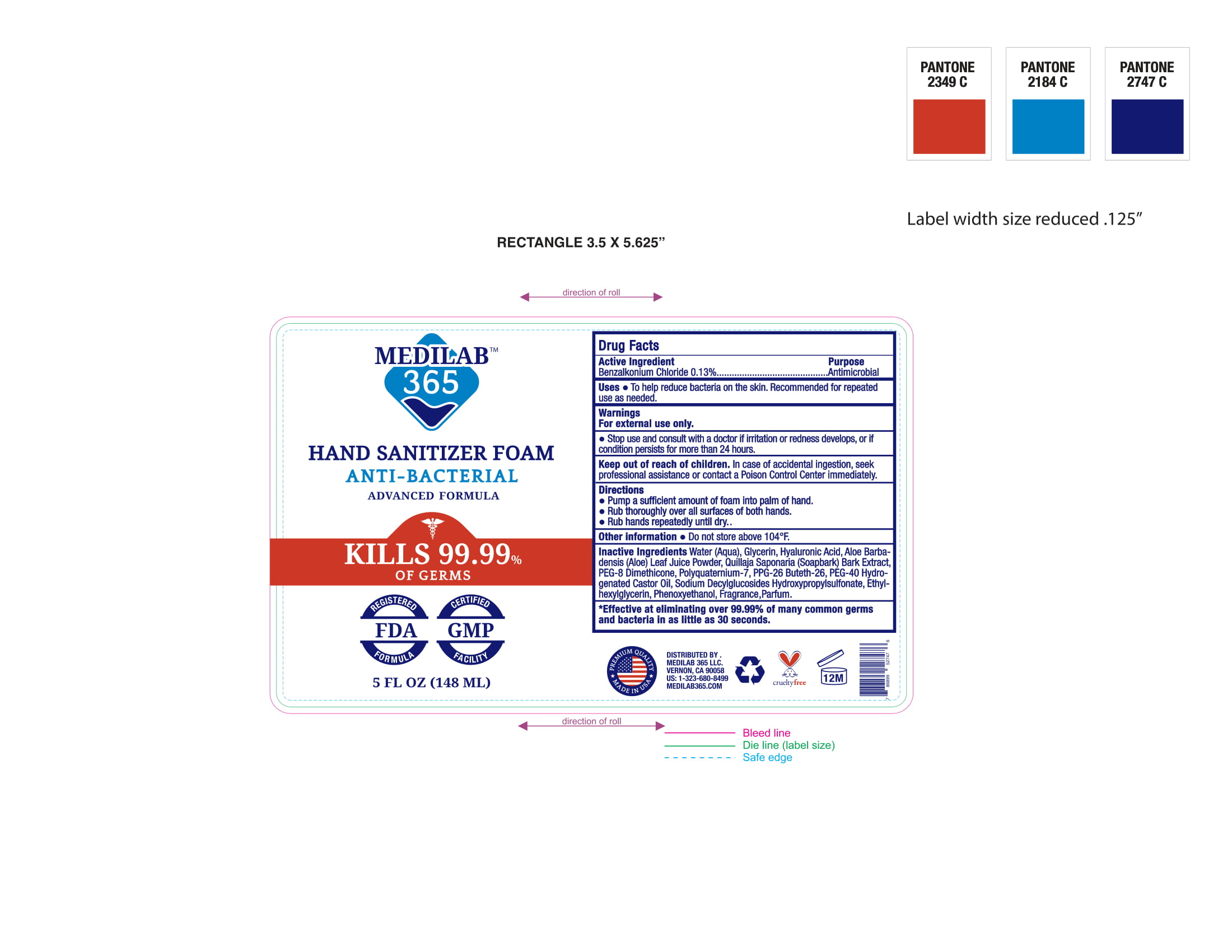 DRUG LABEL: Hand Sanitizer Foam
NDC: 72471-100 | Form: LIQUID
Manufacturer: VMP Cosmetics, LLC
Category: otc | Type: HUMAN OTC DRUG LABEL
Date: 20220122

ACTIVE INGREDIENTS: BENZALKONIUM CHLORIDE 0.13 g/100 g
INACTIVE INGREDIENTS: QUILLAJA SAPONARIA BARK; POLYQUATERNIUM-7 (70/30 ACRYLAMIDE/DADMAC; 1600 KD); POLYOXYL 40 HYDROGENATED CASTOR OIL; ETHYLHEXYLGLYCERIN; ALOE VERA LEAF; SODIUM DECYLGLUCOSIDES HYDROXYPROPYLSULFONATE; PHENOXYETHANOL; GLYCERIN; PEG-8 DIMETHICONE; WATER; HYALURONIC ACID; PPG-26-BUTETH-26

Purpose

Antimicrobial

Uses

*To help decrease bacterial on the skin. Recomended for repeated use as needed.

Warnings

For external use only.

Stop Use

*Stop use and consult with doctor if irritation and redness develops, or if condition persists for more than 24 hours.

Keep out of reach of children

In case of accidental ingestion, seek professional assistance or contact a poison Control Center immediately.

Directions

* Pump a sufficient amount of foam into palm of hand.

* Rub thoroughly over all surfaces of both hands.

* Rub hands repeatedly until dry.

Other Information

Do not store above 104OF.

Inactive Ingredients

Water, Glycerin, Hyaluronic Acid, Aloe Barbadensis Leaf Juice Powder, Quillaja Saponaria (Soapbark) Bark Extract, PEG-8 Dimethicone, Polyquaternium-7, PPG-26 Buteth-26, PEG-40 Hydrogenated Castor Oil, Sodium Decylglucosides Hydroxypropylsulfonate, Ethylhexylglycerin, Phenoxyethanol, Fragrance.

Active Ingredient

Benzalkonium Chloride 0.13%

PDP

MEDILAB

365

HAND SANITIZER FOAM

ANTI-BACTERIAL

ADVANCED FORMULA

KILLS 99.99%

OF GERMS

REGISTERED CERTIFIED

FDA GMP

FORMULA FACILITY

5 FL.OZ (150 ML)